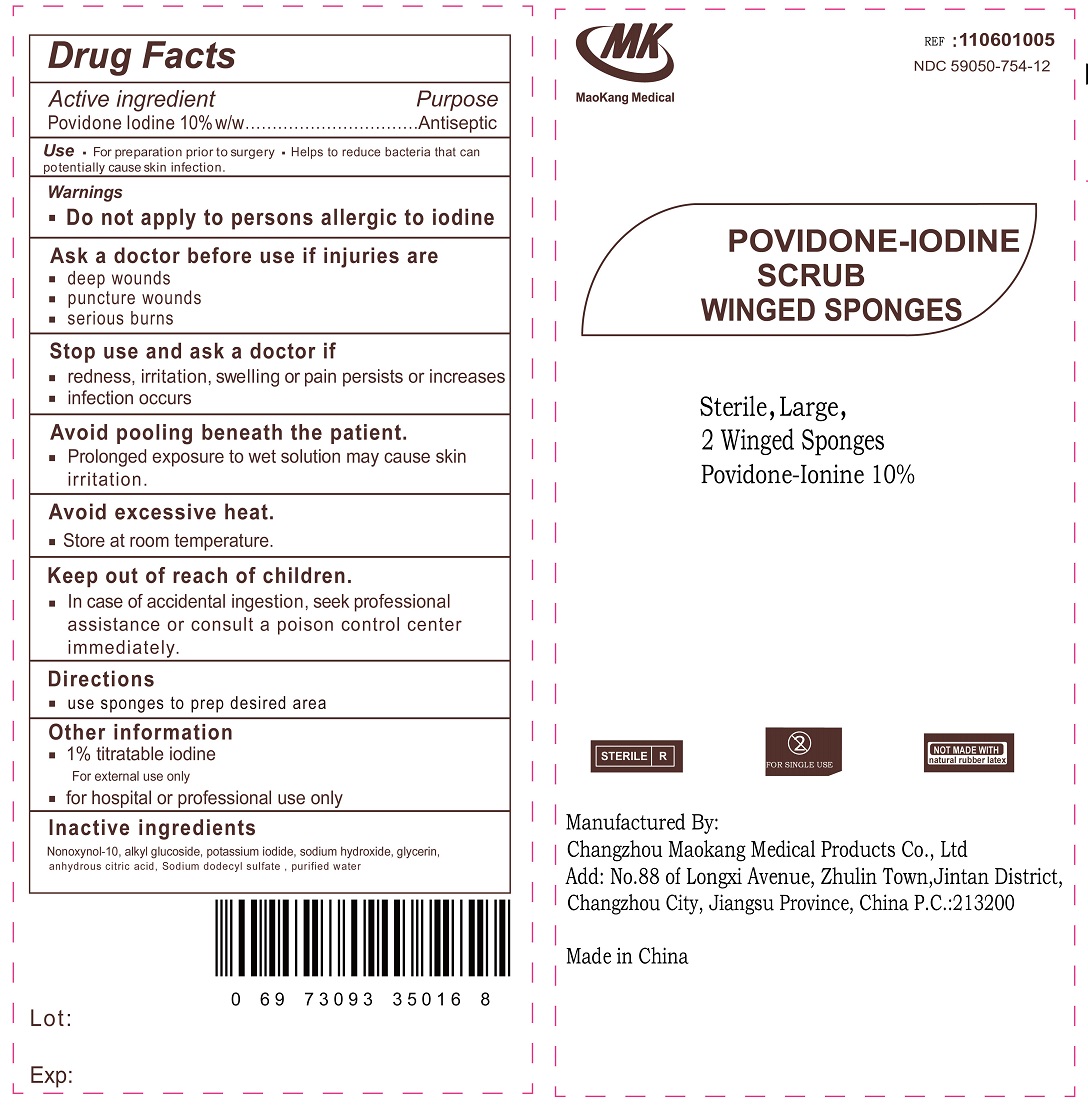 DRUG LABEL: TWO PVP-I SCRUB LARGE WINGED SPONGES
NDC: 59050-754 | Form: SPONGE
Manufacturer: Changzhou Maokang Medical Products Co., Ltd
Category: otc | Type: HUMAN OTC DRUG LABEL
Date: 20231110

ACTIVE INGREDIENTS: POVIDONE-IODINE 100 mg/1 mL
INACTIVE INGREDIENTS: NONOXYNOL-10; POTASSIUM IODIDE; SODIUM HYDROXIDE; GLYCERIN; ANHYDROUS CITRIC ACID; SODIUM LAURYL SULFATE; WATER

TWO PVP-I SCRUB LARGE WINGED SPONGES

Active ingredient

Povidone Iodine 10%w/w

Purpose

Antiseptic

Use

- For preparation prior to surgery
- Helps to reduce bacteria that can potentially cause skin infection.

Warnings

- Do not apply to persons allergic to iodine

Ask a doctor before use if injuries are

- deep wounds
- puncture wounds
- serious burns

Stop use and ask a doctor if

- redness, irritation, swelling or pain persists or increases
- infection occurs

- Prolonged exposure to wet solution may cause skin irritation.

- Store at room temperature.

Avoid pooling beneath the patient.

Avoid excessive heat.

For external use only

Keep out of reach of children.

- In case of accidental ingestion, seek professional assistance or consult a poison control center immediately.

Directions

- use sponge sticks to prep desired area

Other information

- 1% titratable iodine
- for hospital or professional use only

Inactive ingredients

Nonoxynol-10, alkyl glucoside, potassium iodide, sodium hydroxide, glycerin, anhydrous citric acid, Sodium dodecyl sulfate, purifed water